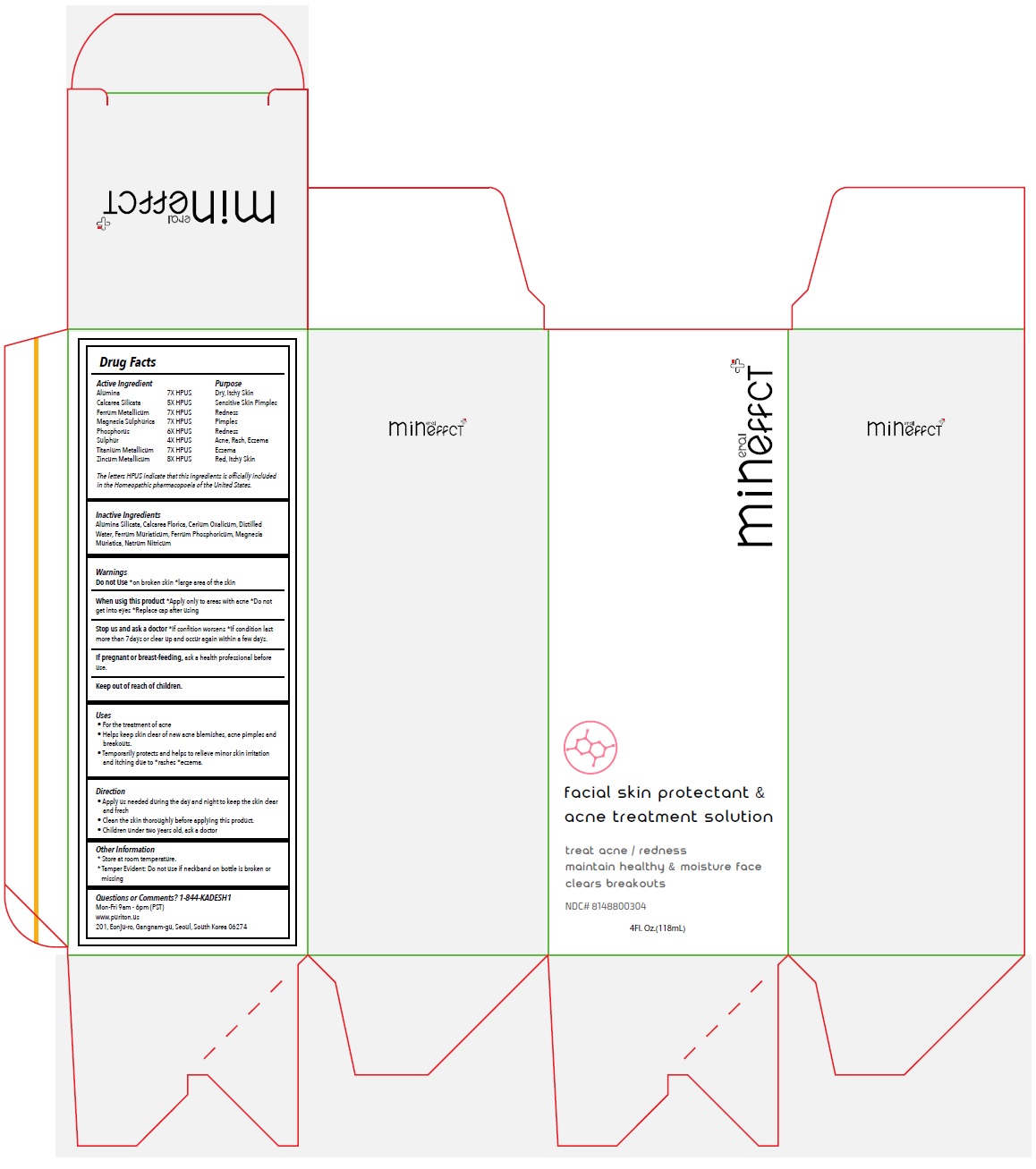 DRUG LABEL: Mineffect facial skin protectant and acne treatment solution
NDC: 81488-003 | Form: SPRAY
Manufacturer: Kadesh Incoporation Co,Ltd
Category: homeopathic | Type: HUMAN OTC DRUG LABEL
Date: 20231031

ACTIVE INGREDIENTS: ALUMINUM OXIDE 7 [hp_X]/118 mL; CALCIUM SILICATE 5 [hp_X]/118 mL; IRON 7 [hp_X]/118 mL; MAGNESIUM SULFATE HEPTAHYDRATE 7 [hp_X]/118 mL; PHOSPHORUS 6 [hp_X]/118 mL; SULFUR 4 [hp_X]/118 mL; TITANIUM 7 [hp_X]/118 mL; ZINC 8 [hp_X]/118 mL
INACTIVE INGREDIENTS: KAOLIN; CALCIUM FLUORIDE; CEROUS OXALATE NONAHYDRATE; WATER; FERRIC CHLORIDE HEXAHYDRATE; FERROSOFERRIC PHOSPHATE; MAGNESIUM CHLORIDE; SODIUM NITRATE

Mineffect facial skin protectant & acne treatment solution

Active Ingredient

Alumina 7X HPUS
Calcarea Silicata 5X HPUS
Ferrum Metallicum 7X HPUS
Magnesia Sulphurica 7X HPUS
Phosphorus 6X HPUS
Sulphur 4X HPUS
Titanium Metallicum 7X HPUS
Zincum Metallicum 8X HPUS

The letters HPUS indicate that this ingredients is officially included in the Homeopathic pharmacopoeia of the United States.

Purpose

Dry, Itchy Skin
Sensitive Skin Pimples
Redness
Pimples
Redness
Acne, Rash, Eczema
Eczema
Red, Itchy Skin

Inactive Ingredients

Alumina Silicata, Calcarea Fluorica, Cerium Oxalicum, Distilled Water, Ferrum Muriaticum, Ferrum Phosphoricum, Magnesia Muriatica, Natrum Nitricum

Warnings

Do not Use*on broken skin *large area of the skin
When using this product*Apply only to areas with acne *Do not get into eyes *Replace cap after using
Stop use and ask a doctor*If condition worsens *If condition last more than 7days or clear up and occur again within a few days.
If pregnant or breast-feeding, ask a health professional before use.

Keep out of reach of children.

Uses

• For the treatment of acne
• Helps keep skin clear of new acne blemishes, acne pimples and breakouts.
• Temporarily protects and helps to relieve minor skin irritation and itching due to *rashes *eczema.

Direction

• Apply as needed during the day and night to keep the skin clear and fresh
• Clean the skin thoroughly before applying this product.
• Children under two years old, ask a doctor

Other Information

* Store at room temperature.
* Tamper Evident: Do not use if neckband on bottle is broken or missing

Questions or Comments? 1-844-KADESH1

Mon-Fri 9am - 6pm (PST)
www.puriton.us
201, Eonju-ro, Gangnam-gu, Seoul, South Korea 06274

treat acne / redness
maintain healthy & moisture face
clears breakouts